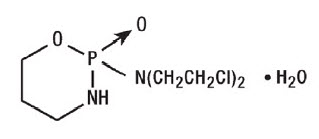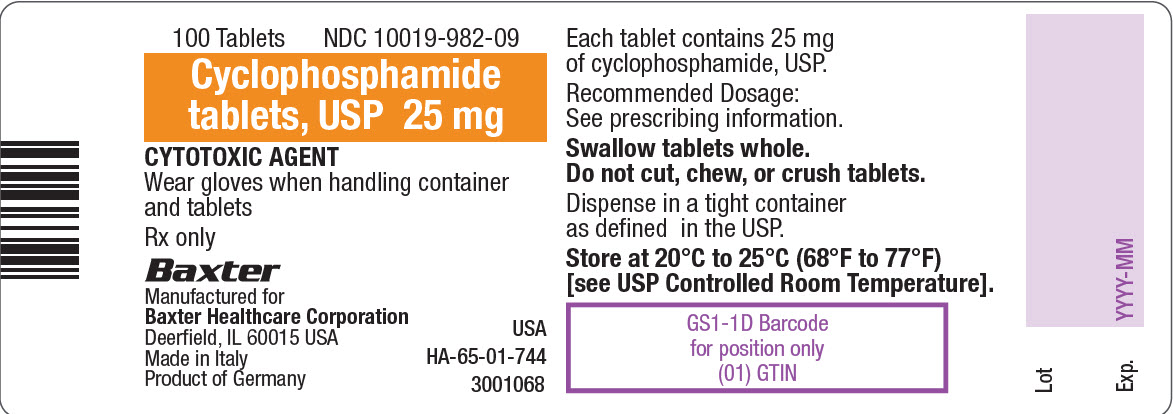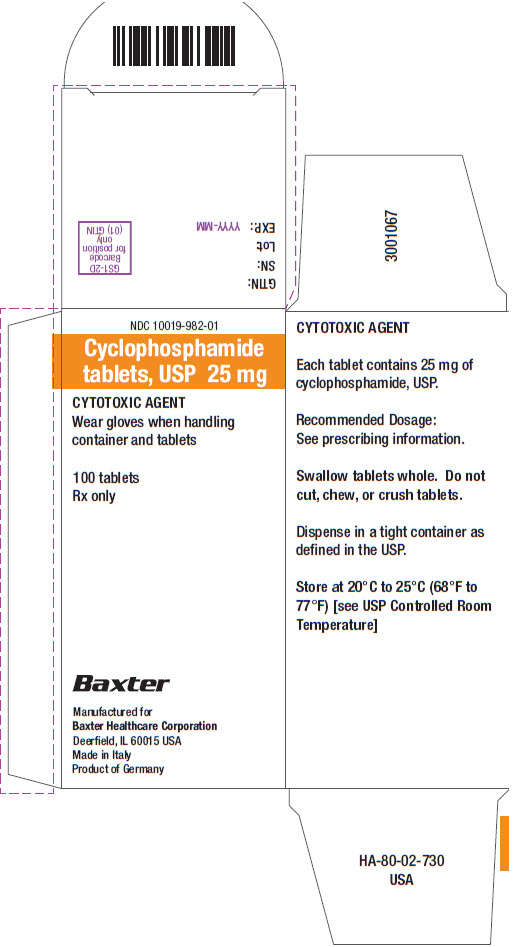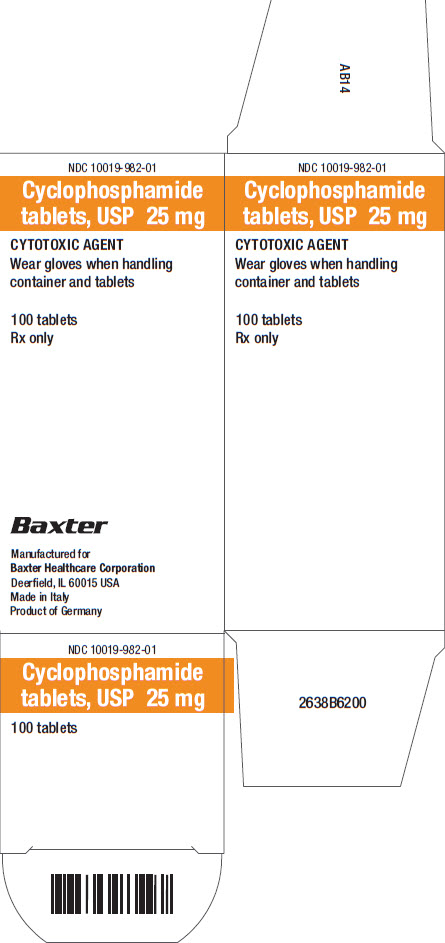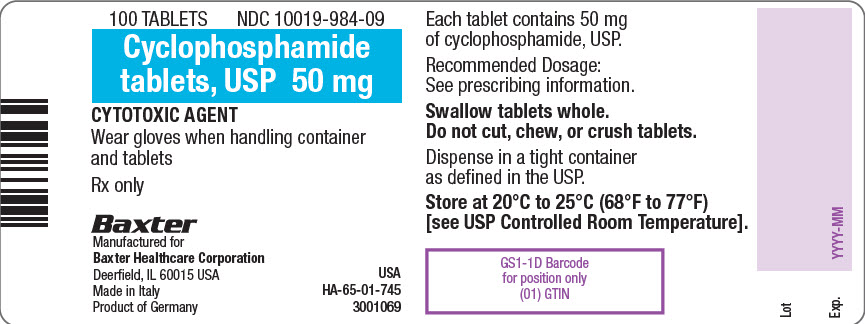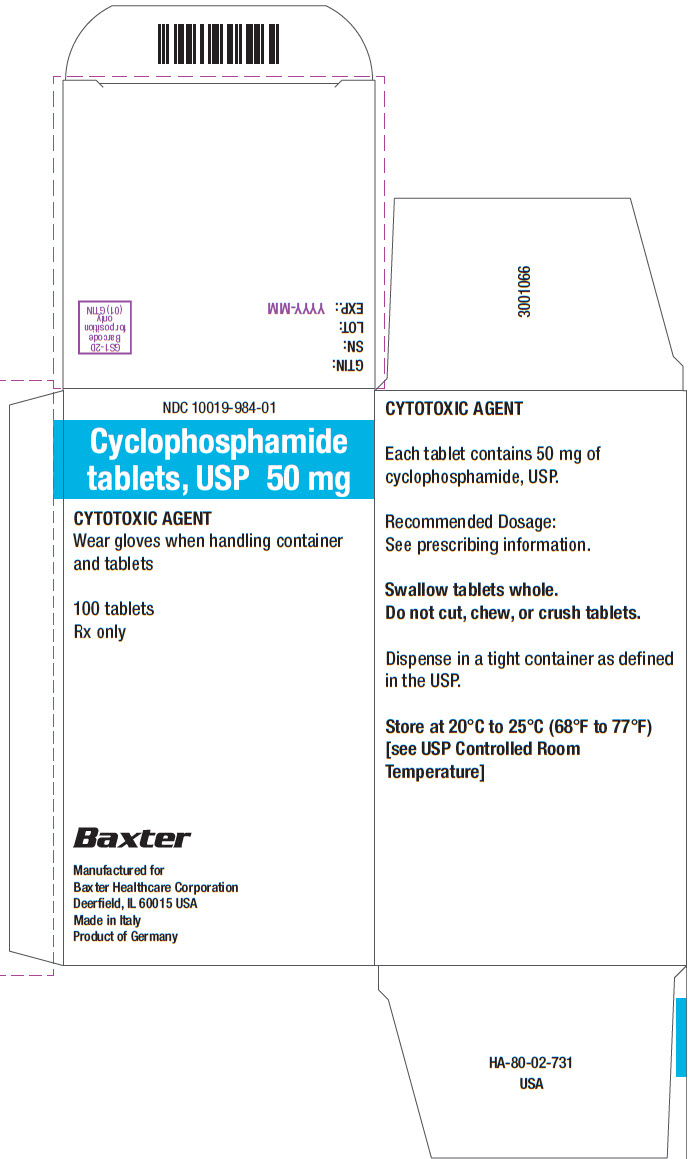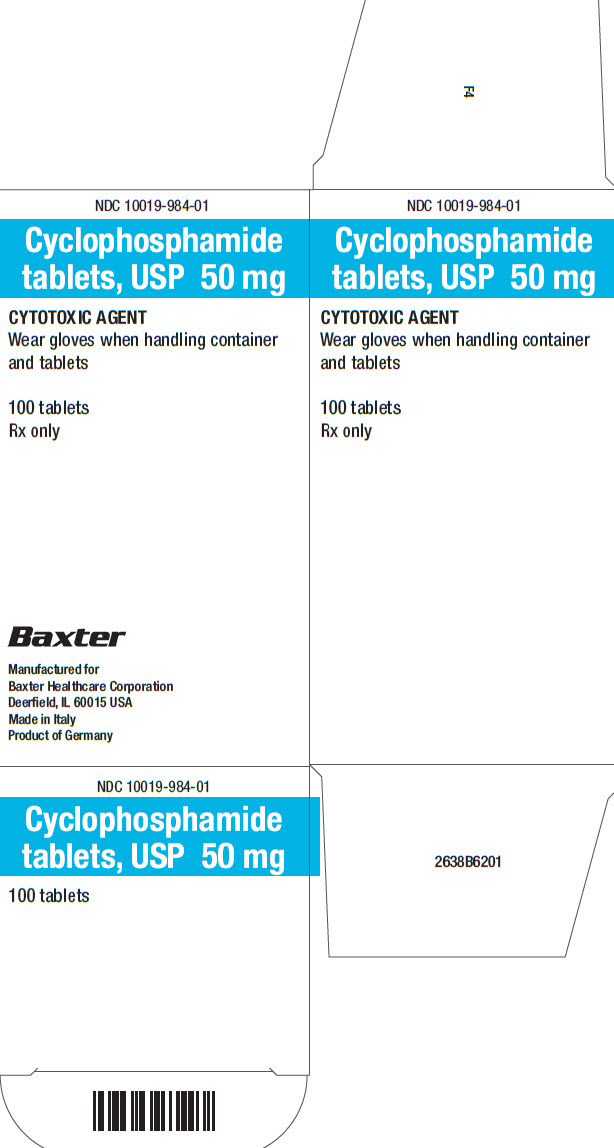 DRUG LABEL: Cyclophosphamide
NDC: 10019-982 | Form: TABLET
Manufacturer: Baxter Healthcare Corporation
Category: prescription | Type: HUMAN PRESCRIPTION DRUG LABEL
Date: 20200807

ACTIVE INGREDIENTS: CYCLOPHOSPHAMIDE 25 mg/1 1

HIGHLIGHTS OF PRESCRIBING INFORMATION

These highlights do not include all the information needed to use CYCLOPHOSPHAMIDE TABLETS safely and effectively. See full prescribing information for CYCLOPHOSPHAMIDE TABLETS.
CYCLOPHOSPHAMIDE tablets, for oral use
Initial U.S. Approval: 1959

RECENT MAJOR CHANGES

Dosage and Administration, Hydration and Important Administration
Instructions (2.1) 08/2020
Warnings and Precautions, Embryo Fetal Toxicity (5.7) 08/2020

1 INDICATIONS AND USAGE

Cyclophosphamide Tablets is an alkylating drug indicated for treatment of:

- Malignant Diseases: malignant lymphomas: Hodgkin’s disease, lymphocytic lymphoma, mixed-cell type lymphoma, histiocytic lymphoma, Burkitt’s lymphoma; multiple myeloma, leukemias, mycosis fungoides, neuroblastoma, adenocarcinoma of ovary, retinoblastoma, breast carcinoma (1.1)
- Minimal Change Nephrotic Syndrome in Pediatric Patients:
  biopsy proven minimal change nephrotic syndrome patients who failed to adequately respond to or are unable to tolerate adrenocorticosteroid therapy (1.2)

Limitations of Use:

The safety and effectiveness for the treatment of nephrotic syndrome in adults or other renal disease has not been established. (1.2)

2 DOSAGE AND ADMINISTRATION

During or immediately after the administration, administer adequate amounts of fluid to reduce the risk of urinary tract toxicity (2.1).

Malignant Diseases: Adult and Pediatric Patients

- Oral: Usually 1 mg per kg to 5 mg per kg once daily for both initial and maintenance dosing. (2.2)

Minimal Change Nephrotic Syndrome in Pediatric Patients

- Recommended oral dose: 2 mg per kg once daily for 8 to 12 weeks (maximum cumulative dose 168 mg per kg). Treatment beyond 90 days increases the probability of sterility in males. (2.3)

3 DOSAGE FORMS AND STRENGTHS

- Tablets: 25 mg and 50 mg (3)

4 CONTRAINDICATIONS

- Hypersensitivity to cyclophosphamide (4)
- Urinary outflow obstruction (4)

5 WARNINGS AND PRECAUTIONS

- Myelosuppression, Immunosuppression, Bone Marrow Failure and Infections – Severe immunosuppression may lead to serious and sometimes fatal infections. Close hematological monitoring is required. (5.1)
- Urinary Tract and Renal Toxicity – Hemorrhagic cystitis, pyelitis, ureteritis, and hematuria can occur. Exclude or correct any urinary tract obstructions prior to treatment. (5.2)
- Cardiotoxicity – Myocarditis, myopericarditis, pericardial effusion, arrythmias and congestive heart failure, which may be fatal, have been reported. Monitor patients, especially those with risk factors for cardiotoxicity or pre-existing cardiac disease. (5.3)
- Pulmonary Toxicity – Pneumonitis, pulmonary fibrosis and pulmonary veno-occlusive disease leading to respiratory failure may occur. Monitor patients for signs and symptoms of pulmonary toxicity. (5.4)
- Secondary malignancies (5.5)
- Veno-occlusive Liver Disease - Fatal outcome can occur. (5.6)
- Embryo-Fetal Toxicity - Can cause fetal harm. Advise patients of potential risk to the fetus and to use effective contraception. (5.7, 8.1, 8.3)

6 ADVERSE REACTIONS

Adverse reactions reported most often include neutropenia, febrile neutropenia, fever, alopecia, nausea, vomiting, and diarrhea. (6.1)

To report SUSPECTED ADVERSE REACTIONS, contact Baxter Healthcare at 1-866-888-2472 or FDA at 1-800-FDA-1088 or www.fda.gov/medwatch.

8 USE IN SPECIFIC POPULATIONS

- Lactation: Advise not to breastfeed. (8.2)
- Females and Males of Reproductive Potential: Verify pregnancy status prior to initiation of Cyclophosphamide Tablets. May impair fertility. (8.3)
- Renal Impairment: Monitor for toxicity in patients with moderate and severe renal impairment. (8.6, 12.3)

FULL PRESCRIBING INFORMATION

1 INDICATIONS AND USAGE

1.1 Malignant Diseases

Cyclophosphamide Tablets is indicated for the treatment of:

- malignant lymphomas (Stages III and IV of the Ann Arbor staging system), Hodgkin’s disease, lymphocytic lymphoma (nodular or diffuse), mixed-cell type lymphoma, histiocytic lymphoma, Burkitt’s lymphoma
- multiple myeloma
- leukemias: chronic lymphocytic leukemia, chronic granulocytic leukemia (it is usually ineffective in acute blastic crisis), acute myelogenous and monocytic leukemia, acute lymphoblastic (stem-cell) leukemia (cyclophosphamide given during remission is effective in prolonging its duration)
- mycosis fungoides (advanced disease)
- neuroblastoma (disseminated disease)
- adenocarcinoma of the ovary
- retinoblastoma
- carcinoma of the breast

Cyclophosphamide, although effective alone in susceptible malignancies, is more frequently used concurrently or sequentially with other antineoplastic drugs.

1.2 Minimal Change Nephrotic Syndrome in Pediatric Patients:

Cyclophosphamide Tablets is indicated for the treatment of biopsy proven minimal change nephrotic syndrome in pediatric patients who failed to adequately respond to or are unable to tolerate adrenocorticosteroid therapy.

Limitations of Use:

The safety and effectiveness of Cyclophosphamide Tablets for the treatment of nephrotic syndrome in adults or other renal disease has not been established.

2 DOSAGE AND ADMINISTRATION

2.1 Hydration and Important Administration Instructions

During or immediately after the administration of Cyclophosphamide Tablets, adequate amounts of fluid should be ingested or infused to force diuresis in order to reduce the risk of urinary tract toxicity. Therefore,

Cyclophosphamide Tablets should be taken in the morning.

Cyclophosphamide Tablets should be swallowed whole. The tablets should not be chewed or crushed.

Cyclophosphamide Tablets is a cytotoxic drug. Follow applicable special handling and disposal procedures.^1 Exposure to broken tablets should be avoided. If contact with broken tablets occurs, wash hands immediately and thoroughly.

2.2 Recommended Dosage for Malignant Diseases

Adults and Pediatric Patients

The recommended dose of Cyclophosphamide Tablets is in the range of 1 mg per kg to 5 mg per kg orally once daily for both initial and maintenance dosing.

Other regimens of oral cyclophosphamide have been reported. Dosages should be adjusted based on evidence of antitumor activity, myelosuppression, or other severe adverse reactions [see Warnings and Precautions (5)].

When cyclophosphamide is included in combined cytotoxic regimens, it may be necessary to reduce the dose of cyclophosphamide, as well as that of the other drugs.

2.3 Recommended Dosage for Minimal Change Nephrotic Syndrome in Pediatric Patients

The recommended dosage of Cyclophosphamide Tablets is 2 mg per kg once daily for 8 to 12 weeks (maximum cumulative dose 168 mg per kg). Treatment beyond 90 days increases the probability of sterility in males [see Use in Specific Populations (8.4)].

3 DOSAGE FORMS AND STRENGTHS

Tablets:

- 25 mg of cyclophosphamide, USP. Tablets are white with blue flecks and imprinted with 25 on one side and BXT on the other.
- 50 mg of cyclophosphamide, USP. Tablets are white with blue flecks and imprinted with 50 on one side and BXT on the other.

4 CONTRAINDICATIONS

Cyclophosphamide Tablets are contraindicated in patients with:

- A history of severe hypersensitivity reactions to cyclophosphamide, any of its metabolites, or to other components of the product. Anaphylactic reactions including death have been reported with cyclophosphamide. Cross-sensitivity with other alkylating agents can occur.
- In patients with urinary outflow obstruction [see Warnings and Precautions (5.2)].

5 WARNINGS AND PRECAUTIONS

5.1 Myelosuppression, Immunosuppression, Bone Marrow Failure and Infections

Cyclophosphamide can cause myelosuppression (leukopenia, neutropenia, thrombocytopenia and anemia), bone marrow failure, and severe immunosuppression which may lead to serious and sometimes fatal infections, including sepsis and septic shock. Latent infections can be reactivated [see Adverse Reactions (6.2)].

Antimicrobial prophylaxis may be indicated in certain cases of neutropenia at the discretion of the managing physician. In case of neutropenic fever, antibiotic therapy is indicated. Antimycotics and/or antivirals may also be indicated.

Monitoring of complete blood counts is essential during cyclophosphamide treatment so that the dose can be adjusted, if needed. Cyclophosphamide should not be administered to patients with neutrophils ≤1,500/mm^3 and platelets < 50,000/mm^3. Cyclophosphamide treatment may not be indicated, or should be interrupted, or the dose reduced, in patients who have or who develop a serious infection. G-CSF may be administered to reduce the risks of neutropenia complications associated with cyclophosphamide use. Primary and secondary prophylaxis with G-CSF should be considered in all patients considered to be at increased risk for neutropenia complications. The nadirs of the reduction in leukocyte count and thrombocyte count are usually reached in weeks 1 and 2 of treatment. Peripheral blood cell counts are expected to normalize after approximately 20 days. Bone marrow failure has been reported. Severe myelosuppression may be expected particularly in patients pretreated with and/or receiving concomitant chemotherapy and/or radiation therapy.

5.2 Urinary Tract and Renal Toxicity

Hemorrhagic cystitis, pyelitis, ureteritis, and hematuria have been reported with cyclophosphamide. Medical and/or surgical supportive treatment may be required to treat protracted cases of severe hemorrhagic cystitis. Discontinue cyclophosphamide therapy in case of severe hemorrhagic cystitis.

Urotoxicity (bladder ulceration, necrosis, fibrosis, contracture and secondary cancer) may require interruption of cyclophosphamide treatment or cystectomy. Urotoxicity can be fatal. Urotoxicity can occur with short-term or long-term use of cyclophosphamide.

Before starting treatment, exclude or correct any urinary tract obstructions [see Contraindications (4)]. Urinary sediment should be checked regularly for the presence of erythrocytes and other signs of urotoxicity and/or nephrotoxicity. Cyclophosphamide should be used with caution, if at all, in patients with active urinary tract infections. Aggressive hydration with forced diuresis and frequent bladder emptying can reduce the frequency and severity of bladder toxicity. Mesna has been used to prevent severe bladder toxicity.

5.3 Cardiotoxicity

Myocarditis, myopericarditis, pericardial effusion including cardiac tamponade, and congestive heart failure, which may be fatal, have been reported with cyclophosphamide therapy

Supraventricular arrhythmias (including atrial fibrillation and flutter) and ventricular arrhythmias (including severe QT prolongation associated with ventricular tachyarrhythmia) have been reported after treatment with regimens that included cyclophosphamide.

The risk of cardiotoxicity may be increased with high doses of cyclophosphamide, in patients with advanced age, and in patients with previous radiation treatment to the cardiac region and/or previous or concomitant treatment with other cardiotoxic agents.

Particular caution is necessary in patients with risk factors for cardiotoxicity and in patients with pre-existing cardiac disease.

Monitor patients with risk factors for cardiotoxicity and with pre-existing cardiac disease.

5.4 Pulmonary Toxicity

Pneumonitis, pulmonary fibrosis, pulmonary veno-occlusive disease and other forms of pulmonary toxicity leading to respiratory failure have been reported during and following treatment with cyclophosphamide. Late onset pneumonitis (greater than 6 months after start of cyclophosphamide) appears to be associated with increased mortality. Pneumonitis may develop years after treatment with cyclophosphamide.

Monitor patients for signs and symptoms of pulmonary toxicity.

5.5 Secondary Malignancies

Cyclophosphamide is genotoxic [see Nonclinical Toxicology (13.1)]. Secondary malignancies (urinary tract cancer, myelodysplasia, acute leukemias, lymphomas, thyroid cancer, and sarcomas) have been reported in patients treated with cyclophosphamide-containing regimens. The risk of bladder cancer may be reduced by prevention of hemorrhagic cystitis.

5.6 Veno-occlusive Liver Disease

Veno-occlusive liver disease (VOD) including fatal outcome has been reported in patients receiving cyclophosphamide-containing regimens. A cytoreductive regimen in preparation for bone marrow transplantation that consists of cyclophosphamide in combination with whole-body irradiation, busulfan, or other agents has been identified as a major risk factor. VOD has also been reported to develop gradually in patients receiving long-term low-dose immunosuppressive doses of cyclophosphamide. Other risk factors predisposing to the development of VOD include preexisting disturbances of hepatic function, previous radiation therapy of the abdomen, and a low performance status.

5.7 Embryo-Fetal Toxicity

Based on its mechanism of action and published reports of effects in pregnant patients or animals, Cyclophosphamide Tablets can cause fetal harm when administered to a pregnant woman [see Use in Specific Populations (8.1), Clinical Pharmacology (12.1), and Nonclinical Toxicology (13.1)]. Exposure to cyclophosphamide during pregnancy may cause birth defects, miscarriage, fetal growth retardation, and fetotoxic effects in the newborn. Cyclophosphamide is teratogenic and embryo-fetal toxic in mice, rats, rabbits and monkeys.

Advise pregnant women and females of reproductive potential of the potential risk to the fetus [see Use in Specific Populations (8.1)]. Verify the pregnancy status of females of reproductive potential prior to initiation of Cyclophosphamide Tablets. Advise females of reproductive potential to use effective contraception during treatment with Cyclophosphamide Tablets and for up to 1 year after completion of therapy. Advise male patients with female partners of reproductive potential to use effective contraception during treatment with Cyclophosphamide Tablets and for 4 months after completion of therapy [see Use in Specific Populations (8.1, 8.3)].

5.8 Infertility

Male and female reproductive function and fertility may be impaired in patients being treated with Cyclophosphamide Tablets. Cyclophosphamide interferes with oogenesis and spermatogenesis. It may cause sterility in both sexes. Development of sterility appears to depend on the dose of cyclophosphamide, duration of therapy, and the state of gonadal function at the time of treatment. Cyclophosphamide-induced sterility may be irreversible in some patients. Advise patients on the potential risks for infertility [see Use in Specific Populations (8.3, 8.4)].

5.9 Impairment of Wound Healing

Cyclophosphamide may interfere with normal wound healing.

5.10 Hyponatremia

Hyponatremia associated with increased total body water, acute water intoxication, and a syndrome resembling SIADH (syndrome of inappropriate secretion of antidiuretic hormone), which may be fatal, has been reported.

6 ADVERSE REACTIONS

The following adverse reactions are discussed in more detail in other sections of the labeling.

- Hypersensitivity [see Contraindications (4)]
- Myelosuppression, Immunosuppression, Bone Marrow Failure, and Infections [see Warnings and Precautions (5.1)]
- Urinary Tract and Renal Toxicity [see Warnings and Precautions (5.2)]
- Cardiotoxicity [see Warnings and Precautions (5.3)]
- Pulmonary Toxicity [see Warnings and Precautions (5.4)]
- Secondary Malignancies [see Warnings and Precautions (5.5)]
- Veno-occlusive Liver Disease [see Warnings and Precautions (5.6)]
- Infertility [see Warnings and Precautions (5.8) and Use in Specific Populations (8.3, 8.4)]
- Impaired Wound Healing [see Warnings and Precautions (5.9)]
- Hyponatremia [see Warnings and Precautions (5.10)]

6.1 Common Adverse Reactions

Hematopoietic system:
Neutropenia occurs in patients treated with cyclophosphamide. The degree of neutropenia is particularly important because it correlates with a reduction in resistance to infections. Fever without documented infection has been reported in neutropenic patients.

Gastrointestinal system:
Nausea and vomiting occur with cyclophosphamide therapy. Anorexia and, less frequently, abdominal discomfort or pain and diarrhea may occur. There are isolated reports of hemorrhagic colitis, oral mucosal ulceration and jaundice occurring during therapy.

Skin and its structures:
Alopecia occurs in patients treated with cyclophosphamide. Skin rash occurs occasionally in patients receiving the drug. Pigmentation of the skin and changes in nails can occur.

6.2 Postmarketing Experience

The following adverse reactions have been identified from clinical trials or post-marketing surveillance. Because they are reported from a population from unknown size, precise estimates of frequency cannot be made.

Cardiac: cardiac arrest, ventricular fibrillation, ventricular tachycardia, cardiogenic shock, pericardial effusion (progressing to cardiac tamponade), myocardial hemorrhage, myocardial infarction, cardiac failure (including fatal outcomes), cardiomyopathy, myocarditis, pericarditis, carditis, atrial fibrillation, supraventricular arrhythmia, ventricular arrhythmia, bradycardia, tachycardia, palpitations, QT prolongation.

Congenital, Familial and Genetic: intra-uterine death, fetal malformation, fetal growth retardation, fetal toxicity (including myelosuppression, gastroenteritis).

Ear and Labyrinth: deafness, hearing impaired, tinnitus.

Endocrine: water intoxication.

Eye: visual impairment, conjunctivitis, lacrimation.

Gastrointestinal: gastrointestinal hemorrhage, acute pancreatitis, colitis, enteritis, cecitis, stomatitis, constipation, parotid gland inflammation.

General Disorders and Administrative Site Conditions: multiorgan failure, general physical deterioration, influenza-like illness, injection/infusion site reactions (thrombosis, necrosis, phlebitis, inflammation, pain, swelling, erythema), pyrexia, edema, chest pain, mucosal inflammation, asthenia, pain, chills, fatigue, malaise, headache.

Hematologic: myelosuppression, bone marrow failure, disseminated intravascular coagulation and hemolytic uremic syndrome (with thrombotic microangiopathy).

Hepatic: veno-occlusive liver disease, cholestatic hepatitis, cytolytic hepatitis, hepatitis, cholestasis; hepatotoxicity with hepatic failure, hepatic encephalopathy, ascites, hepatomegaly, blood bilirubin increased, hepatic function abnormal, hepatic enzymes increased.

Immune: immunosuppression, anaphylactic shock and hypersensitivity reaction.

Infections: The following manifestations have been associated with myelosuppression and immunosuppression caused by cyclophosphamide: increased risk for and severity of pneumonias (including fatal outcomes), other bacterial, fungal, viral, protozoal and, parasitic infections; reactivation of latent infections, (including viral hepatitis, tuberculosis), pneumocystis jiroveci, herpes zoster, strongyloides, sepsis and septic shock.

Investigations: blood lactate dehydrogenase increased, C-reactive protein increased.

Metabolism and Nutrition: hyponatremia, fluid retention, blood glucose increased, blood glucose decreased.

Musculoskeletal and Connective Tissue: rhabdomyolysis, scleroderma, muscle spasms, myalgia, arthralgia.

Neoplasms: acute leukemia, myelodysplastic syndrome, lymphoma, sarcomas, renal cell carcinoma, renal pelvis cancer, bladder cancer, ureteric cancer, thyroid cancer.

Nervous System: encephalopathy, convulsion, dizziness, neurotoxicity has been reported and manifested as reversible posterior leukoencephalopathy syndrome, myelopathy, peripheral neuropathy, polyneuropathy, neuralgia, dysesthesia, hypoesthesia, paresthesia, tremor, dysgeusia, hypogeusia, parosmia.

Pregnancy: premature labor.

Psychiatric: confusional state.

Renal and Urinary: renal failure, renal tubular disorder, renal impairment, nephropathy toxic, hemorrhagic cystitis, bladder necrosis, cystitis ulcerative, bladder contracture, hematuria, nephrogenic diabetes insipidus, atypical urinary bladder epithelial cells.

Reproductive System: infertility, ovarian failure, ovarian disorder, amenorrhea, oligomenorrhea, testicular atrophy, azoospermia, oligospermia.

Respiratory: pulmonary veno-occlusive disease, acute respiratory distress syndrome, interstitial lung disease as manifested by respiratory failure (including fatal outcomes), obliterative bronchiolitis, organizing pneumonia, alveolitis allergic, pneumonitis, pulmonary hemorrhage; respiratory distress, pulmonary hypertension, pulmonary edema, pleural effusion, bronchospasm, dyspnea, hypoxia, cough, nasal congestion, nasal discomfort, oropharyngeal pain, rhinorrhea.

Skin and Subcutaneous Tissue: toxic epidermal necrolysis, Stevens-Johnson syndrome, erythema multiforme, palmar-plantar erythrodysesthesia syndrome, radiation recall dermatitis, toxic skin eruption, urticaria, dermatitis, blister, pruritus, erythema, nail disorder, facial swelling, hyperhidrosis.

Tumor lysis syndrome: like other cytotoxic drugs, cyclophosphamide may induce tumor-lysis syndrome and hyperuricemia in patients with rapidly growing tumors.

Vascular: pulmonary embolism, venous thrombosis, vasculitis, peripheral ischemia, hypertension, hypotension, flushing, hot flush.

7 DRUG INTERACTIONS

Cyclophosphamide is a pro-drug that is activated by cytochrome P450s [see Clinical Pharmacology (12.3)].

An increase of the concentration of cytotoxic metabolites may occur with:

- Protease inhibitors: Concomitant use of protease inhibitors may increase the concentration of cytotoxic metabolites. Use of protease inhibitor-based regimens was found to be associated with a higher Incidence of infections and neutropenia in patients receiving cyclophosphamide, doxorubicin, and etoposide (CDE) than use of a Non-Nucleoside Reverse Transcriptase Inhibitor-based regimen.

Combined or sequential use of cyclophosphamide and other agents with similar toxicities can potentiate toxicities.

- Increased hematotoxicity and/or immunosuppression may result from a combined effect of cyclophosphamide and, for example:
  - ACE inhibitors: ACE inhibitors can cause leukopenia.
  - Natalizumab
Paclitaxel: Increased hematotoxicity has been reported when cyclophosphamide was administered after paclitaxel infusion.
Thiazide diuretics
  Zidovudine
  Increased cardiotoxicity may result from a combined effect of cyclophosphamide and, for example:
- Anthracyclines
- Cytarabine
- Pentostatin
- Radiation therapy of the cardiac region
- Trastuzumab
- Increased pulmonary toxicity may result from a combined effect of cyclophosphamide and, for example:
- Amiodarone
- G-CSF, GM-CSF (granulocyte colony-stimulating factor, granulocyte macrophage colony-stimulating factor): Reports suggest an increased risk of pulmonary toxicity in patients treated with cytotoxic chemotherapy that includes cyclophosphamide and G-CSF or GMCSF.
- Increased nephrotoxicity may result from a combined effect of cyclophosphamide and, for example:
  Amphotericin B
  Indomethacin: Acute water intoxication has been reported with concomitant use of indomethacin
  Increase in other toxicities:
  Azathioprine: Increased risk of hepatotoxicity (liver necrosis)
  Busulfan: Increased incidence of hepatic veno-occlusive disease and mucositis has been reported.
  Protease inhibitors: Increased incidence of mucositis
Increased risk of hemorrhagic cystitis may result from a combined effect of cyclophosphamide and
  past or concomitant radiation treatment.

Etanercept: In patients with Wegener’s granulomatosis, the addition of etanercept to standard treatment, including cyclophosphamide, was associated with a higher incidence of non-cutaneous malignant solid tumors.

Metronidazole: Acute encephalopathy has been reported in a patient receiving cyclophosphamide and metronidazole. Causal association is unclear. In an animal study, the combination of cyclophosphamide with metronidazole was associated with increased cyclophosphamide toxicity.

Tamoxifen: Concomitant use of tamoxifen and chemotherapy may increase the risk of thromboembolic complications.

Coumarins: Both increased and decreased warfarin effect have been reported in patients receiving warfarin and cyclophosphamide.

Cyclosporine: Lower serum concentrations of cyclosporine have been observed in patients receiving a combination of cyclophosphamide and cyclosporine than in patients receiving only cyclosporine. This interaction may result in an increased incidence of graft-versus-host disease.

Depolarizing muscle relaxants: Cyclophosphamide treatment causes a marked and persistent inhibition of cholinesterase activity. Prolonged apnea may occur with concurrent depolarizing muscle relaxants (e.g., succinylcholine). If a patient has been treated with cyclophosphamide within 10 days of general anesthesia, alert the anesthesiologist.

8 USE IN SPECIFIC POPULATIONS

8.1 Pregnancy

Risk Summary
Based on its mechanism of action and published reports of effects in pregnant patients or animals, Cyclophosphamide Tablets can cause fetal harm when administered to a pregnant woman [see Clinical Pharmacology (12.1) and Nonclinical Toxicology (13.1)]. Exposure to cyclophosphamide during pregnancy may cause fetal malformations, miscarriage, fetal growth retardation, and toxic effects in the newborn [see Data]. Cyclophosphamide is teratogenic and embryo-fetal toxic in mice, rats, rabbits and monkeys. Advise pregnant women and females of reproductive potential of the potential risk to the fetus.

The estimated background risk of major birth defects and miscarriage for the indicated population is unknown. In the U.S. general population, the estimated background risk of major birth defects is 2%-4% and of miscarriage is 15%-20% of clinically recognized pregnancies.

Data
Human Data
Malformations of the skeleton, palate, limbs and eyes as well as miscarriage have been reported after exposure to cyclophosphamide in the first trimester. Fetal growth retardation and toxic effects manifesting in the newborn, including leukopenia, anemia, pancytopenia, severe bone marrow hypoplasia, and gastroenteritis have been reported after exposure to cyclophosphamide.

Animal Data
Administration of cyclophosphamide to pregnant mice, rats, rabbits and monkeys during the period of organogenesis at doses at or below the dose in patients based on body surface area resulted in various malformations, which included neural tube defects, limb and digit defects and other skeletal anomalies, cleft lip and palate, and reduced skeletal ossification.

8.2 Lactation

Risk Summary
Cyclophosphamide is present in breast milk. Neutropenia, thrombocytopenia, low hemoglobin, and diarrhea have been reported in infants breastfed by women treated with cyclophosphamide. Because of the potential for serious adverse reactions in a breastfed child from cyclophosphamide, advise lactating women not to breastfeed during treatment and for 1 week after the last dose.

8.3 Females and Males of Reproductive Potential

Pregnancy Testing
Verify the pregnancy status of females of reproductive potential prior to the initiation of Cyclophosphamide Tablets [see Use in Specific Populations (8.1)].

Contraception
Females
Cyclophosphamide can cause fetal harm. Advise females of reproductive potential to use effective contraception during treatment with Cyclophosphamide Tablets and for up to 1 year after completion of therapy [see Use in Specific Populations (8.1)].

Males
Based on findings in genetic toxicity and animal reproduction studies, advise male patients with female partners of reproductive potential to use effective contraception during treatment with Cyclophosphamide Tablets and for at least 4 months after completion of therapy [see Use in Specific Populations (8.1) and Nonclinical Toxicology (13.1)].

Infertility
Females
Amenorrhea, transient or permanent, associated with decreased estrogen and increased gonadotropin secretion develops in a proportion of women treated with cyclophosphamide. Affected patients generally resume regular menses within a few months after cessation of therapy. The risk of premature menopause with cyclophosphamide increases with age. Oligomenorrhea has also been reported in association with cyclophosphamide treatment.

Animal data suggest an increased risk of failed pregnancy and malformations may persist after discontinuation of cyclophosphamide as long as oocytes/follicles exist that were exposed to cyclophosphamide during any of their maturation phases. The exact duration of follicular development in humans is not known, but may be longer than 12 months [see Nonclinical Toxicology (13.1)].

Males
Men treated with cyclophosphamide may develop oligospermia or azoospermia which are normally associated with increased gonadotropin but normal testosterone secretion.

8.4 Pediatric Use

Pre-pubescent girls treated with cyclophosphamide generally develop secondary sexual characteristics normally and have regular menses. Ovarian fibrosis with apparently complete loss of germ cells after prolonged cyclophosphamide treatment in late pre-pubescence has been reported. Girls treated with cyclophosphamide who have retained ovarian function after completing treatment are at increased risk of developing premature menopause.

Pre-pubescent boys treated with cyclophosphamide develop secondary sexual characteristics normally, but may have oligospermia or azoospermia and increased gonadotropin secretion. Some degree of testicular atrophy may occur. Cyclophosphamide-induced azoospermia is reversible in some patients, though the reversibility may not occur for several years after cessation of therapy.

8.5 Geriatric Use

There is insufficient data from clinical studies of cyclophosphamide available for patients 65 years of age and older to determine whether they respond differently than younger patients. In general, dose selection for an elderly patient should be cautious, usually starting at the low end of the dosing range, reflecting the greater frequency of decreased hepatic, renal, or cardiac functioning, and of concomitant disease or other drug therapy.

8.6 Use in Patients with Renal Impairment

In patients with severe renal impairment, decreased renal excretion may result in increased plasma levels of cyclophosphamide and its metabolites. This may result in increased toxicity [see Clinical Pharmacology (12.3)]. Monitor patients with severe renal impairment (CrCl =10 mL/min to 24 mL/min) for signs and symptoms of toxicity.

Cyclophosphamide and its metabolites are dialyzable although there are probably quantitative differences depending upon the dialysis system being used. In patients requiring dialysis, use of a consistent interval between cyclophosphamide administration and dialysis should be considered.

8.7 Use in Patients with Hepatic Impairment

Patients with severe hepatic impairment have reduced conversion of cyclophosphamide to the active 4-hydroxyl metabolite, potentially reducing efficacy [see Clinical Pharmacology (12.3)].

10 OVERDOSAGE

No specific antidote for cyclophosphamide is known.

Overdosage should be managed with supportive measures, including appropriate treatment for any concurrent infection, myelosuppression, or cardiac toxicity should it occur.

Serious consequences of overdosage include manifestations of dose dependent toxicities such as myelosuppression, urotoxicity, cardiotoxicity (including cardiac failure), veno-occlusive hepatic disease, and stomatitis [see Warnings and Precautions (5.1, 5.2, 5.3, and 5.6)].

Patients who received an overdose should be closely monitored for the development of toxicities, and hematologic toxicity in particular.

Cyclophosphamide and its metabolites are dialyzable. Therefore, rapid hemodialysis is indicated when treating any suicidal or accidental overdose or intoxication.

Cystitis prophylaxis with mesna may be helpful in preventing or limiting urotoxic effects with cyclophosphamide overdose.

11 DESCRIPTION

Cyclophosphamide is a synthetic antineoplastic drug chemically related to the nitrogen mustards. The chemical name for cyclophosphamide is 2-[bis(2-chloroethyl)amino]tetrahydro-2H-1,3,2-oxazaphosphorine 2-oxide monohydrate, and has the following structural formula:

Cyclophosphamide has a molecular formula of C7H15Cl2N2O2P•H2O and a molecular weight of 279.1. Cyclophosphamide is soluble in water, saline, or ethanol.

Cyclophosphamide Tablets, USP are for oral use and contain 25 mg or 50 mg cyclophosphamide (anhydrous). Inactive ingredients in Cyclophosphamide Tablets are: acacia, FD&C Blue No. 1, D&C Yellow No. 10 Aluminum Lake, lactose, magnesium stearate, starch, stearic acid and talc.

12 CLINICAL PHARMACOLOGY

12.1 Mechanism of Action

The mechanism of action is thought to involve cross-linking of tumor cell DNA.

12.2 Pharmacodynamics

Cyclophosphamide is biotransformed principally in the liver to active alkylating metabolites by a mixed function microsomal oxidase system. These metabolites interfere with the growth of susceptible rapidly proliferating malignant cells.

12.3 Pharmacokinetics

Absorption
After oral administration, peak concentrations of cyclophosphamide occurred at one hour. Area under the curve ratio for the drug after oral and IV administration (AUCpo : AUCiv) ranged from 0.87 to 0.96.

Distribution
Approximately 20% of cyclophosphamide is protein bound, with no dose dependent changes. Some metabolites are protein bound to an extent greater than 60%. Volume of distribution approximates total body water (30 to 50 L).

Metabolism
The liver is the major site of cyclophosphamide activation. Approximately 75% of the administered dose of cyclophosphamide is activated by hepatic microsomal cytochrome P450s including CYP2A6, 2B6, 3A4, 3A5, 2C9, 2C18 and 2C19, with 2B6 displaying the highest 4-hydroxylase activity. Cyclophosphamide is activated to form 4-hydroxycyclophosphamide, which is in equilibrium with its ring-open tautomer aldophosphamide. 4-hydroxycyclophosphamide and aldophosphamide can undergo oxidation by aldehyde dehydrogenases to form the inactive metabolites 4-ketocyclophosphamide and carboxyphosphamide, respectively. Aldophosphamide can undergo β-elimination to form active metabolites phosphoramide mustard and acrolein. This spontaneous conversion can be catalyzed by albumin and other proteins. Less than 5% of cyclophosphamide may be directly detoxified by side chain oxidation, leading to the formation of inactive metabolites 2-dechloroethylcyclophosphamide. At high doses, the fraction of parent compound cleared by 4-hydroxylation is reduced resulting in non-linear elimination of cyclophosphamide in patients. Cyclophosphamide appears to induce its own metabolism. Auto-induction results in an increase in the total clearance, increased formation of 4-hydroxyl metabolites and shortened t1/2 values following repeated administration at 12- to 24-hour interval.

Elimination
Cyclophosphamide is primarily excreted as metabolites. 10 to 20% is excreted unchanged in the urine and 4% is excreted in the bile following IV administration.

Special Populations

Renal Impairment
The pharmacokinetics of cyclophosphamide were determined following one-hour intravenous infusion to renally impaired patients. The results demonstrated that the systemic exposure to cyclophosphamide increased as the renal function decreased. Mean dose-corrected AUC increased by 38% in the moderate renal group, (Creatinine clearance (CrCl of 25 to 50 mL/min), by 64% in the severe renal group (CrCl of 10 to 24 mL/min) and by 23% in the hemodialysis group (CrCl of < 10 mL/min) compared to the control group. The increase in exposure was significant in the severe group (p>0.05); thus, patients with severe renal impairment should be closely monitored for toxicity [see Use in Specific Populations (8.6)].

The dialyzability of cyclophosphamide was investigated in four patients on long-term hemodialysis. Dialysis clearance calculated by arterial-venous difference and actual drug recovery in dialysate averaged 104 mL/min, which is in the range of the metabolic clearance of 95 mL/min for the drug. A mean of 37% of the administered dose of cyclophosphamide was removed during hemodialysis. The elimination half-life (t1/2) was 3.3 hours in patients during hemodialysis, a 49% reduction of the 6.5 hours to t1/2 reported in uremic patients. Reduction in t1/2, larger dialysis clearance than metabolic clearance, high extraction efficiency, and significant drug removal during dialysis, suggest that cyclophosphamide is dialyzable.

Hepatic Impairment
Total body clearance (CL) of cyclophosphamide is decreased by 40% in patients with severe hepatic impairment and elimination half-life (t1/2) is prolonged by 64%. Mean CL and t1/2 were 45 ± 8.6 L/kg and 12.5 ± 1.0 hours respectively, in patients with severe hepatic impairment and 63 ± 7.6 L/kg and 7.6 ± 1.4 hours respectively in the control group [see Use in Specific Populations (8.7)].

13 NONCLINICAL TOXICOLOGY

13.1 Carcinogenesis, Mutagenesis, Impairment of Fertility

Cyclophosphamide administered by different routes, including intravenous, subcutaneous or intraperitoneal injection, or in drinking water, caused tumors in both mice and rats. In addition to leukemia and lymphoma, benign and malignant tumors were found at various tissue sites, including urinary bladder, mammary gland, lung, liver, and injection site [see Warnings and Precautions (5.5)].

Cyclophosphamide was mutagenic and clastogenic in multiple in vitro and in vivo genetic toxicology studies.

Cyclophosphamide is genotoxic in male and female germ cells. Animal data indicate that exposure of oocytes to cyclophosphamide during follicular development may result in a decreased rate of implantations and viable pregnancies, and in an increased risk of malformations. Male mice and rats treated with cyclophosphamide show alterations in male reproductive organs (e.g., decreased weights, atrophy, changes in spermatogenesis), and decreases in reproductive potential (e.g., decreased implantations and increased post-implantation loss) and increases in fetal malformations when mated with untreated females [see Use in Specific Populations (8.3)].

15 REFERENCES

1. OSHA Hazardous Drugs. OSHA. http://www.osha.gov/SLTC/hazardousdrugs/index.html.

16 HOW SUPPLIED/STORAGE AND HANDLING

Tablets:

- 25 mg of cyclophosphamide, USP. Tablets are white with blue flecks and imprinted with 25 on one side and BXT on the other side.
NDC 10019-982-01: Carton containing bottle of 100 tablets (NDC 10019-982-09)
- 50 mg of cyclophosphamide, USP. Tablets are white with blue flecks and imprinted with 50 on one side and BXT on the other side.
NDC 10019-984-01: Carton containing bottle of 100 tablets (NDC 10019-984-09)

Store tablets at 20°C to 25°C (68°F to77°F); excursions permitted between 15°C to 30°C (59°F to 86°F) [see USP Controlled Room Temperature].

Cyclophosphamide is an antineoplastic product. Follow special handling and disposal procedures.1

17 PATIENT COUNSELING INFORMATION

Advise the patient of the following:

Myelosuppression, Immunosuppression, and Infections

- Inform patients of the possibility of myelosuppression, immunosuppression, and infections. Explain the need for routine blood cell counts. Instruct patients to monitor their temperature frequently and immediately report any occurrence of fever [see Warnings and Precautions (5.1)].

Urinary Tract and Renal Toxicity

- Advise the patient to report urinary symptoms (patients should report if their urine has turned a pink or red color) and the need for increasing fluid intake and frequent voiding [see Warnings and Precautions (5.2)].

Cardiotoxicity

- Advise patients to contact a health care professional immediately for any of the following: new onset or worsening shortness of breath, cough, swelling of the ankles/legs, palpitations, weight gain of more than 5 pounds in 24 hours, dizziness or loss of consciousness [see Warnings and Precautions (5.3)].

Pulmonary Toxicity

- Warn patients of the possibility of developing non-infectious pneumonitis. Advise patients to report promptly any new or worsening respiratory symptoms [see Warnings and Precautions (5.4)].

Embryo-Fetal Toxicity

- Inform female patients of the risk to a fetus and potential loss of the pregnancy. Advise females to inform their healthcare provider of a known or suspected pregnancy [see Warnings and Precautions (5.7) and Use in Specific Populations (8.1)].
- Advise female patients of reproductive potential to use effective contraception during treatment and for up to 1 year after completion of therapy [see Warnings and Precautions (5.7) and Use in Specific Populations (8.1, 8.3)].
- Advise male patients with female partners of reproductive potential to use effective contraception during treatment and for up to 4 months after completion of therapy [see Warnings and Precautions (5.7) and Use in Specific Populations (8.1, 8.3)].

Lactation

- Advise lactating women not to breastfeed during treatment and for 1 week after the last dose of Cyclophosphamide Tablets [see Use in Specific Populations (8.2)].

Infertility

- Cyclophosphamide Tablets may impair fertility in males and females of reproductive potential [see Warnings and Precautions (5.8) and Use in Specific Populations (8.3, 8.4)].

Common Adverse Reactions

- Explain to patients that side effects such as nausea, vomiting, stomatitis, impaired wound healing, amenorrhea, premature menopause, sterility and hair loss may be associated with cyclophosphamide administration. Other undesirable effects (including, e.g., dizziness, blurred vision, visual impairment) could affect the ability to drive or use machines [see Adverse Reactions (6.1, 6.2)].

Hydration and Important Administration Instructions

- Advise the patient that during or immediately after the administration, adequate amounts of fluid are required to reduce the risk of urinary tract toxicity [see Dosage and Administration (2.1)].
- Instruct the patient to swallow Cyclophosphamide Tablets whole. Do not cut, chew, or crush tablets [see Dosage and Administration (2.1)].
- Advise caregivers to wear gloves when handling bottles containing Cyclophosphamide Tablets and avoid exposure to broken tablets. If contact with broken tablets occurs, wash hands immediately and thoroughly [see Dosage and Administration (2.1)].

Baxter

Manufactured for
Baxter Healthcare Corporation
Deerfield, IL 60015 USA
Made in Italy
Product of Germany

Baxter is a registered trademark of Baxter
International Inc.

HA-30-01-863

Revised August 2020

PACKAGE/LABEL PRINCIPAL DISPLAY PANEL

Container Label

Barcode

100 Tablets
NDC 10019-982-09

Cyclophosphamide
tablets, USP 25 mg

CYTOTOXIC AGENT
Wear gloves when handling container
and tablets

Rx only

Baxter Logo
Manufactured for
Baxter Healthcare Corporation
Deerfield, IL 60015 USA
Made in Italy
Product of Germany

Each tablet contains 25 mg
of cyclophosphamide, USP.

Recommended Dosage:
See prescribing information.

Swallow tablets whole.
Do not cut, chew, or crush tablets.

Dispense in a tight container
as defined in the USP.

Store at or below 25°C (77°F)
[see USP Controlled Room Temperature].

GS1-1D Barcode
for position only
(01) GTIN

USA
HA-65-01-744
3001068

Lot
Exp.
YYYY-MM

Carton Label

GTIN:
S/N:
LOT:
EXP.:
YYYY-MM

GS1-2D
Barcode
for position
only

(01) GTIN

Barcode

NDC 10019-982-01

Cyclophosphamide
tablets, USP 25 mg

CYTOTOXIC AGENT
Wear gloves when handling
container and tablets

100 tablets
Rx only

Baxter Logo
Manufactured for
Baxter Healthcare Corporation
Deerfield, IL 60015 USA
Made in Italy
Product of Germany

3001067

CYTOTOXIC AGENT

Each tablet contains 25 mg
of cyclophosphamide, USP.

Recommended Dosage:
See prescribing information.

Swallow tablets whole. Do not
cut, chew, or crush tablets.

Dispense in a tight container
as defined in the USP.

Store at 20°C to 25°C (68°F to
77°) [see USP Controlled Room
Temperature]

HA-80-02-730
USA

NDC 10019-982-01

Cyclophosphamide
tablets, USP 25 mg

CYTOTOXIC AGENT
Wear gloves when handling
container and tablets

100 tablets
Rx only

Baxter Logo
Manufactured for
Baxter Healthcare Corporation
Deerfield, IL 60015 USA
Made in Italy
Product of Germany

NDC 10019-982-01

Cyclophosphamide
tablets, USP 25 mg

100 tablets

Barcode

AB14

NDC 10019-982-01

Cyclophosphamide
tablets, USP 25 mg

CYTOTOXIC AGENT
Wear gloves when handling
container and tablets

100 tablets
Rx only

2638B6200

Container Label

Barcode

100 TABLETS
NDC 10019-984-09

Cyclophosphamide
tablets, USP 50 mg

CYTOTOXIC AGENT
Wear gloves when handling container
and tablets

Rx only

Baxter Logo
Manufactured for
Baxter Healthcare Corporation
Deerfield, IL 60015 USA
Made in Italy
Product of Germany

Each tablet contains 50 mg
of cyclophosphamide, USP.

Recommended Dosage:
See prescribing information.

Swallow tablets whole.
Do not cut, chew, or crush tablets.

Dispense in a tight container
as defined in the USP.

Store at or below 25°C (77°F)
[see USP Controlled Room Temperature].

GS1-1D Barcode
for position only
(01) GTIN

USA
HA-65-01-745
3001069

Lot
Exp.
YYYY-MM

Carton Label

GTIN:
S/N:
LOT:
EXP.:
YYYY-MM

GS1-2D
Barcode
for position
only
(01) GTIN

Barcode

NDC 10019-984-01

Cyclophosphamide
tablets, USP 50 mg

CYTOTOXIC AGENT
Wear gloves when handling container
and tablets

100 tablets
Rx only

Baxter Logo
Manufactured for
Baxter Healthcare Corporation
Deerfield, IL 60015 USA
Made in Italy
Product of Germany

3001066

CYTOTOXIC AGENT

Each tablet contains 50 mg of
cyclophosphamide, USP.

Recommended Dosage:
See prescribing information.

Swallow tablets whole.
Do not cut, chew, or crush tablets.

Dispense in a tight container as
defined in the USP.

Store at 20°C to 25°C (68°F to
77°) [see USP Controlled Room
Temperature]

HA-80-02-731
USA

NDC 10019-984-01

Cyclophosphamide
tablets, USP 50 mg

CYTOTOXIC AGENT
Wear gloves when handling container
and tablets

100 tablets
Rx only

Baxter Logo
Manufactured for
Baxter Healthcare Corporation
Deerfield, IL 60015 USA
Made in Italy
Product of Germany

NDC 10019-984-01

Cyclophosphamide
tablets, USP 50 mg

100 tablets

Barcode

F4

NDC 10019-984-01

Cyclophosphamide
tablets, USP 50 mg

CYTOTOXIC AGENT
Wear gloves when handling container
and tablets

100 tablets
Rx only

2638B6201